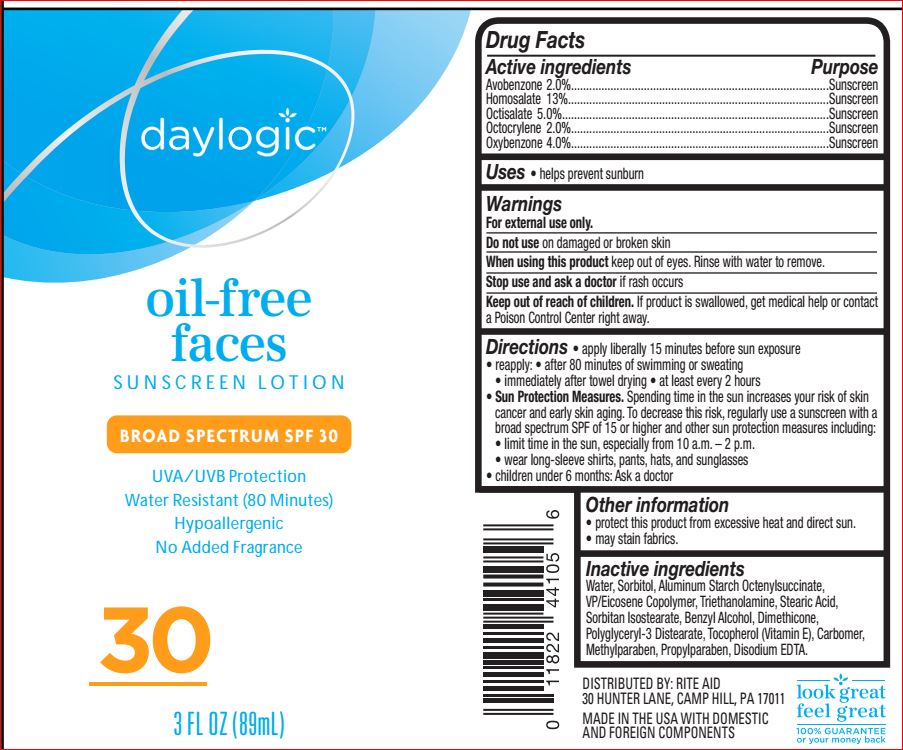 DRUG LABEL: Oil Free Faces Sunscreen SPF 30
NDC: 11822-1239 | Form: LOTION
Manufacturer: Rite Aid
Category: otc | Type: HUMAN OTC DRUG LABEL
Date: 20180622

ACTIVE INGREDIENTS: Avobenzone 2 g/100 mL; Homosalate 13 g/100 mL; Octisalate 5 g/100 mL; Octocrylene 2 g/100 mL; Oxybenzone 4 g/100 mL
INACTIVE INGREDIENTS: Aluminum Starch Octenylsuccinate; Benzyl Alcohol; CARBOMER HOMOPOLYMER TYPE C (ALLYL PENTAERYTHRITOL CROSSLINKED); Dimethicone; EDETATE DISODIUM; Methylparaben; Polyglyceryl-3 Distearate; Propylparaben; Sorbitan Isostearate; Sorbitol; Stearic Acid; Tocopherol; TROLAMINE; EICOSYL POVIDONE; Water

Drug Facts

Active ingredients Purpose
Avobenzone 2.0%.....................................................................................Sunscreen
Homosalate 13%......................................................................................Sunscreen
Octisalate 5.0%........................................................................................Sunscreen
Octocrylene 2.0%.....................................................................................Sunscreen
Oxybenzone 4.0%.....................................................................................Sunscreen

INDICATIONS AND USAGE

Uses • helps prevent sunburn

Warnings
For external use only.
Do not use on damaged or broken skin
When using this product keep out of eyes. Rinse with water to remove.
Stop use and ask a doctor if rash occurs
Keep out of reach of children. If product is swallowed, get medical help or contact
a Poison Control Center right away

Directions

• apply liberally 15 minutes before sun exposure
• reapply: • after 80 minutes of swimming or sweating
• immediately after towel drying • at least every 2 hours
• Sun Protection Measures. Spending time in the sun increases your risk of skin
cancer and early skin aging. To decrease this risk, regularly use a sunscreen with a
broad spectrum SPF of 15 or higher and other sun protection measures including:
• limit time in the sun, especially from 10 a.m. – 2 p.m.
• wear long-sleeve shirts, pants, hats, and sunglasses
• children under 6 months: Ask a doctor

Other information
• protect this product from excessive heat and direct sun.
• may stain fabrics.

Inactive ingredients

Aluminum Starch Octenylsuccinate
Benzyl Alcohol
Carbomer
Dimethicone
Disodium EDTA
Methylparaben
Polyglyceryl-3 Distearate
Propylparaben
Sorbitan Isostearate
Sorbitol
Stearic Acid
Tocopherol
Triethanolamine
VP/Eicosene Copolymer
Water